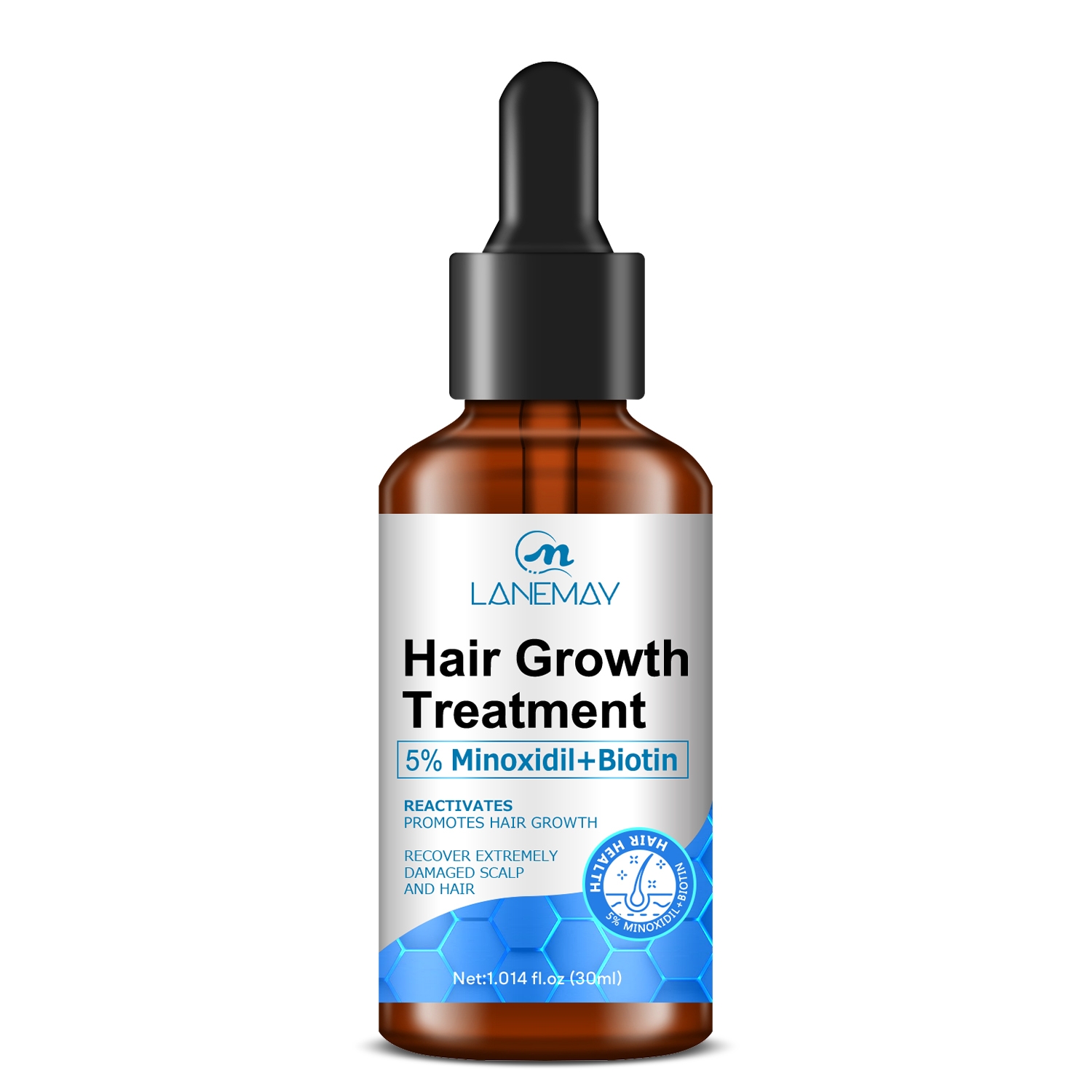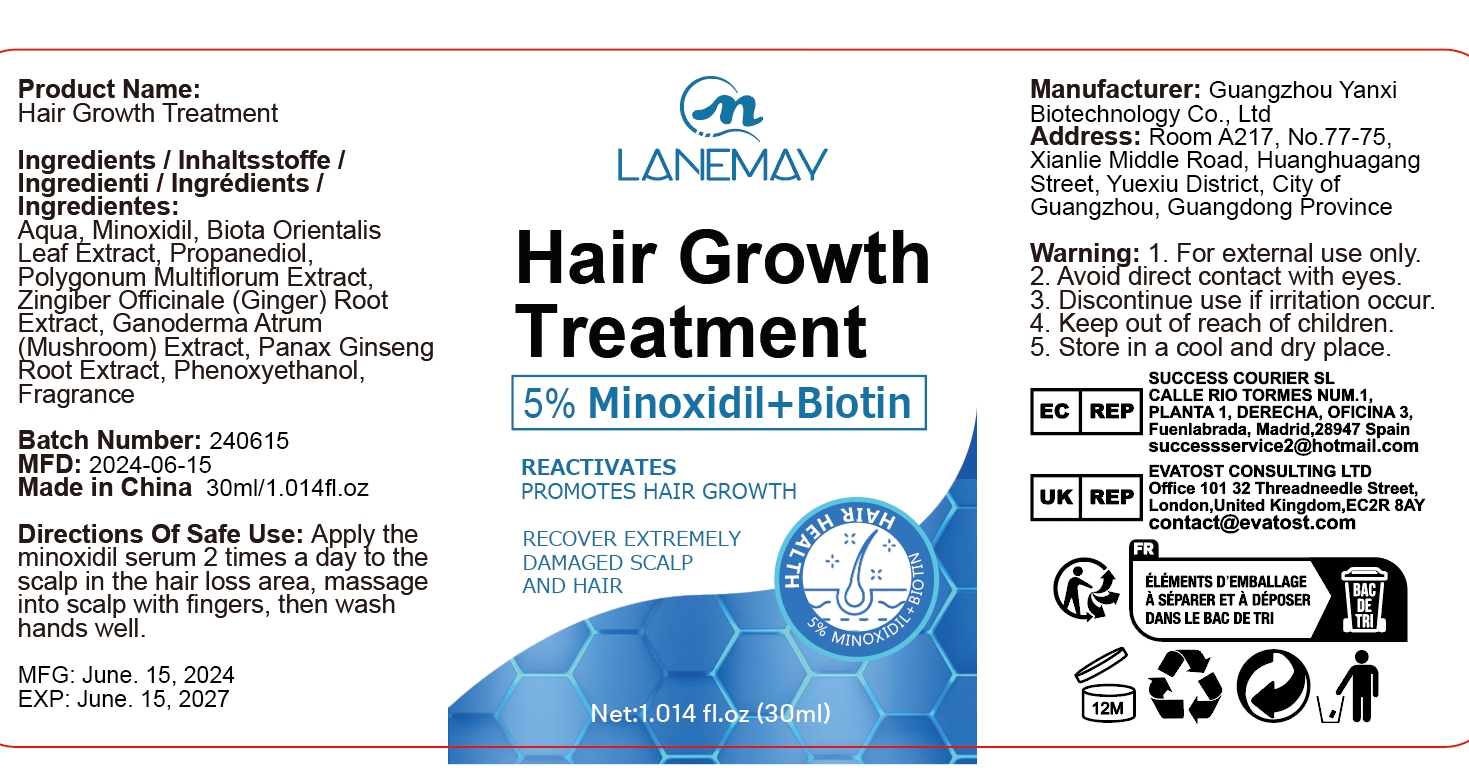 DRUG LABEL: Hair Growth Treatment
NDC: 84025-079 | Form: OIL
Manufacturer: Guangzhou Yanxi Biotechnology Co.. Ltd
Category: otc | Type: HUMAN OTC DRUG LABEL
Date: 20240722

ACTIVE INGREDIENTS: PROPANEDIOL 3 mg/30 mL; MINOXIDIL 5 mg/30 mL
INACTIVE INGREDIENTS: WATER

DOSAGE AND ADMINISTRATION

Works on the scalp and hair

WARNINGS

Keep out of children

INACTIVE INGREDIENT

Aqua

Keep out oif children

PURPOSE

Grow Hair Nourish Scalp

INDICATIONS AND USAGE

Treating Hair Loss and Rough Hair

PURPOSE

Nourishes the scalp and treats hair loss